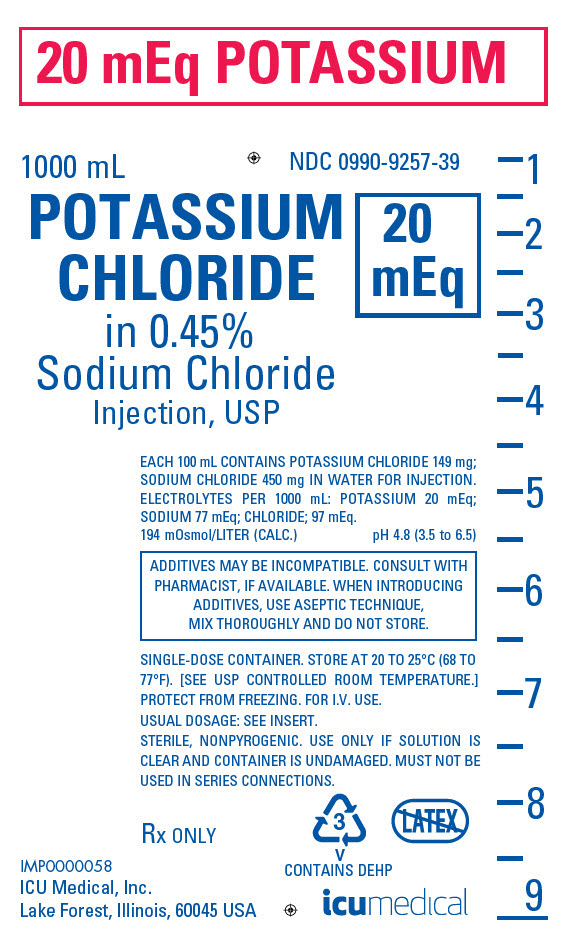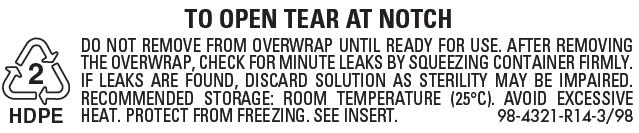 DRUG LABEL: Potassium Chloride in Sodium Chloride
NDC: 0990-9257 | Form: INJECTION, SOLUTION
Manufacturer: ICU Medical Inc.
Category: prescription | Type: HUMAN PRESCRIPTION DRUG LABEL
Date: 20251102

ACTIVE INGREDIENTS: SODIUM CHLORIDE 4.5 g/1000 mL; POTASSIUM CHLORIDE 1.49 g/1000 mL

Potassium Chloride in Sodium Chloride Injection, USP

Flexible Plastic Container

Rx only

DESCRIPTION

Potassium Chloride in Sodium Chloride Injection, USP is a sterile, nonpyrogenic, solution for fluid and electrolyte replenishment in a single dose container for intravenous administration. It contains no antimicrobial agents. Composition, osmolarity, pH and ionic concentration are shown in Table 1.

Table 1:
20 mEq/ L Potassium Chloride in 0.45% Sodium Chloride Inj., USP |  | Composition (g/L) |  | Calculated Osmolarity (mOsmol/L) | pH (range) | Ionic Concentrations (mEq/L)
NDC No. | Size (mL) | Sodium Chloride (NaCl) | Potassium Chloride (KCl) | Calculated Osmolarity (mOsmol/L) | pH (range) | Sodium (Na+) | Potassium (K+) | Chloride (Cl-)
0409-9257-39 | 1000 | 4.5 | 1.49 | 194 | 4.8 (3.5 to 6.5) | 77 | 20 | 97
0990-9257-39 | 1000 | 4.5 | 1.49 | 194 | 4.8 (3.5 to 6.5) | 77 | 20 | 97

The flexible plastic container is fabricated from a specially formulated polyvinyl chloride (PL 146 Plastic). The amount of water that can permeate from inside the container into the overwrap is insufficient to affect the solution significantly. Solutions in contact with the plastic container can leach out certain of its chemical components in very small amounts within the expiration period. However, the safety of the plastic has been confirmed in tests in animals according to USP biological tests for plastic containers.

CLINICAL PHARMACOLOGY

Potassium Chloride in Sodium Chloride Injection, USP has value as a source of water and electrolytes. It is capable of inducing diuresis depending on the clinical condition of the patient.

INDICATIONS AND USAGE

Potassium Chloride in Sodium Chloride Injection, USP is indicated as a source of water and electrolytes.

CONTRAINDICATIONS

Potassium Chloride in Sodium Chloride Injection, USP is contraindicated in patients with:

- Known hypersensitivity to potassium chloride and/or sodium chloride (see WARNINGS).
- Clinically significant hyperkalemia (see WARNINGS).

WARNINGS

Hypersensitivity

Hypersensitivity and infusion reactions, including anaphylaxis and chills, have been reported with products containing potassium chloride and sodium chloride. Stop the infusion immediately if signs or symptoms of a hypersensitivity or infusion reaction develops. Appropriate therapeutic countermeasures must be instituted as clinically indicated.

Electrolyte Imbalances

Hyperkalemia

Potassium-containing solutions, including Potassium Chloride in Sodium Chloride Injection, USP may increase the risk of hyperkalemia. Hyperkalemia can be asymptomatic and manifest only by increased serum potassium concentrations and/or characteristic electrocardiographic (ECG) changes. Cardiac conduction disorders (including complete heart block) and other cardiac arrhythmias, some fatal, can develop at any time during hyperkalemia. Continuous electrocardiogram (ECG) monitoring may be necessary to aid in the detection of cardiac arrhythmias due to hyperkalemia (see ADVERSE REACTIONS).

To avoid life threatening hyperkalemia, do not administer Potassium Chloride in Sodium Chloride Injection, USP as an intravenous push (i.e., intravenous injection manually with a syringe connected to the intravenous access) without a quantitative infusion device.

Patients at increased risk of developing hyperkalemia and cardiac arrhythmias include those:

- with conditions predisposing to hyperkalemia and/or associated with increased sensitivity to potassium, such as patients with severe renal impairment, acute dehydration, extensive tissue injury or burns, certain cardiac disorders such as congestive heart failure or atrioventricular (AV) block (especially if they receive digoxin).
- who are at risk of experiencing hyperosmolality, acidosis, or undergoing correction of alkalosis (conditions associated with a shift of potassium from intracellular to extracellular space).
- treated concurrently or recently with agents or products that can cause or increase the risk of hyperkalemia (see DRUG INTERACTIONS).
- with cardiac arrhythmias.

Avoid use of Potassium Chloride in Sodium Chloride Injection, USP in patients with, or at risk for, hyperkalemia. If use cannot be avoided, use a product with a low amount of potassium chloride, infuse slowly and monitor serum potassium concentrations and ECGs.

Hypernatremia and Hyperchloremia

Electrolyte imbalances such as hypernatremia, hyperchloremia, and metabolic acidosis may occur with Potassium Chloride in Sodium Chloride Injection, USP.

Conditions that may increase the risk of hypernatremia, fluid overload and edema (central and peripheral), include patients with: primary hyperaldosteronism; secondary hyperaldosteronism associated with, for example, hypertension, congestive heart failure, liver disease (including cirrhosis), renal disease (including renal artery stenosis, nephrosclerosis); and pre-eclampsia.

Certain medications, such as corticosteroids or corticotropin, may also increase risk of sodium and fluid retention, see DRUG INTERACTIONS.

Avoid Potassium Chloride in Sodium Chloride Injection, USP in patients with, or at risk for, hypernatremia or hyperchloremia. If use cannot be avoided, monitor serum sodium and chloride concentrations and acid-base balance.

Rapid correction of hypernatremia is potentially dangerous with risk of serious neurologic complications. Excessively rapid correction of hypernatremia is also associated with a risk for serious neurologic complications such as osmotic demyelination syndrome (ODS) with risk of seizures and cerebral edema.

Hyponatremia

Potassium Chloride in Sodium Chloride Injection, USP may cause hyponatremia.

Hyponatremia can lead to acute hyponatremic encephalopathy characterized by headache, nausea, seizures, lethargy, and vomiting. Patients with brain edema are at particular risk of severe, irreversible and life-threatening brain injury.

The risk of hospital-acquired hyponatremia is increased in patients with cardiac or pulmonary failure, and in patients with non-osmotic vasopressin release (including SIADH) treated with high volume of hypotonic Potassium Chloride in Sodium Chloride Injection, USP.

The risk for hyponatremia is increased in pediatric patients, elderly patients, postoperative patients, those with psychogenic polydipsia, and in patients treated with medications that increase the risk of hyponatremia (such as diuretics, certain antiepileptic and psychotropic medications). See DRUG INTERACTIONS.

Patients at increased risk for developing complications of hyponatremia such as hyponatremic encephalopathy, include pediatric patients, women (in particular, premenopausal women), patients with hypoxemia, and patients with underlying central nervous system disease. Avoid Potassium Chloride in Sodium Chloride Injection, USP in patients with or at risk for hyponatremia. If use cannot be avoided, monitor serum sodium concentrations.

Rapid correction of hyponatremia is potentially dangerous with risk of serious neurologic complications. Brain adaptations reducing risk of cerebral edema make the brain vulnerable to injury when chronic hyponatremia is too rapidly corrected, which is known as osmotic demyelination syndrome (ODS). To avoid complications, monitor serum sodium and chloride concentrations, fluid status, acid-base balance, and signs of neurologic complications.

Fluid Overload

Depending on the volume and rate of infusion, and the patient's underlying clinical condition, the intravenous administration of Potassium Chloride in Sodium Chloride Injection, USP can cause electrolyte disturbances such as overhydration/hypervolemia and congested states including central (e.g., pulmonary edema) and peripheral edema.

Avoid Potassium Chloride in Sodium Chloride Injection, USP in patients with or at risk for fluid and/or solute overloading. If use cannot be avoided, monitor fluid balance, electrolyte concentrations and acid base balance as needed and especially during prolonged use.

PRECAUTIONS

Patients with Severe Renal Impairment

Administration of sodium and potassium in patients with or at risk of severe renal impairment, may result in hypernatremia, hyperkalemia and/or fluid overload (see WARNINGS). Avoid Potassium Chloride in Sodium Chloride Injection, USP in patients with severe renal impairment. If use cannot be avoided, monitor patients with severe renal impairment for development of these adverse reactions.

Drug Interactions

Lithium

Renal sodium and lithium clearance may be increased during administration of Potassium Chloride in Sodium Chloride Injection, USP and result in decreased lithium concentrations. Monitor serum lithium concentrations during concomitant use.

Other Products that Cause Hyperkalemia

Administration of Potassium Chloride in Sodium Chloride Injection, USP in patients treated concurrently or recently with products that are associated with hyperkalemia increases the risk of severe and potentially fatal hyperkalemia, in particular in the presence of other risk factors for hyperkalemia. Avoid use of Potassium Chloride in Sodium Chloride Injection, USP in patients receiving such products (e.g., potassium sparing diuretics, angiotensin-converting enzyme inhibitors, angiotensin receptor blockers, or the immunosuppressants cyclosporine and tacrolimus). If use cannot be avoided, monitor serum potassium concentrations.

Other Products that Affect Fluid and/or Electrolyte Balance

Administration of Potassium Chloride in Sodium Chloride Injection, USP in patients treated concomitantly with medications associated with sodium and fluid retention may increase the risk of hypernatremia and volume overload. Avoid use of Potassium Chloride in Sodium Chloride Injection, USP in patients receiving such products, such as corticosteroids or corticotropin. If use cannot be avoided, monitor serum electrolytes, fluid balance, and acid-base balance.

Other Drugs that Increase the Risk of Hyponatremia

Administration of Potassium Chloride in Sodium Chloride Injection, USP in patients treated concomitantly with medications associated with hyponatremia may increase the risk of developing hyponatremia.

Avoid use of Potassium Chloride in Sodium Chloride Injection, USP in patients receiving products, such as diuretics, and certain antiepileptic and psychotropic medications. Drugs that increase the vasopressin effect reduce renal electrolyte free water excretion and may also increase the risk of hyponatremia following treatment with intravenous fluids. If use cannot be avoided, monitor serum sodium concentrations.

Pregnancy

There are no adequate and well controlled studies from the use of Potassium Chloride in Sodium Chloride Injection, USP in pregnant or lactating women and animal reproduction studies have not been conducted with this drug. Therefore, it is also not known whether Potassium Chloride in Sodium Chloride Injection, USP can cause fetal harm when administered to a pregnant woman or can affect reproduction capacity. Potassium Chloride in Sodium Chloride Injection, USP should be given to a pregnant woman only if the potential benefit justifies the potential risk to the fetus.

Nursing Mothers

It is not known whether this drug is excreted in human milk. Because many drugs are excreted in human milk, caution should be exercised when Potassium Chloride in Sodium Chloride Injection, USP is administered to a nursing mother.

Pediatric Use

The use of Potassium Chloride in Sodium Chloride Injection, USP in pediatric patients is based on clinical practice. (See DOSAGE AND ADMINISTRATION). Safety and effectiveness of Potassium Chloride in Sodium Chloride Injection, USP in pediatric patients have not been established by adequate and well-controlled studies.

Pediatric patients are at increased risk of developing hyponatremia as well as for developing encephalopathy as a complication of hyponatremia (see WARNINGS).

Geriatric Use

Geriatric patients are at increased risk of developing electrolyte imbalances. Potassium Chloride in Sodium Chloride Injection, USP is known to be substantially excreted by the kidney, and the risk of toxic reactions to this drug may be greater in patients with impaired renal function. Therefore, dose selection for an elderly patient should be cautious, usually starting at the low end of the dosing range, reflecting the greater frequency of decreased hepatic, renal, or cardiac function, and of concomitant disease or other drug therapy. Consider monitoring renal function in elderly patients.

ADVERSE REACTIONS

The following adverse reactions associated with the use of Potassium Chloride in Sodium Chloride Injection, USP were identified in clinical trials or postmarketing reports. Because postmarketing reactions were reported voluntarily from a population of uncertain size, it is not always possible to estimate their frequency, reliably, or to establish a causal relationship to drug exposure.

- General disorders and administration site conditions: Chills, and infusion site pain. Hypersensitivity reactions: generalized papules and erythema, rash, fever, vomiting, hypertension, tachycardia.
- Metabolism and nutrition disorders: Hyperkalemia, hyponatremia, hypernatremia, hyperchloremia acidosis, fluid overload.
- Cardiac disorders: Cardiac arrest as a manifestation of rapid intravenous administration and/or of hyperkalemia.
- Nervous System Disorders: Hyponatremic encephalopathy.

If an adverse reaction does occur, discontinue the infusion, evaluate the patient, institute appropriate therapeutic countermeasures and save the remainder of the fluid for examination if deemed necessary.

OVERDOSAGE

An increased infusion rate of Potassium Chloride in Sodium Chloride Injection, USP can cause:

- hyperkalemia, manifestations may include disturbances in cardiac conduction and arrhythmias, including bradycardia, heart block, asystole, ventricular tachycardia, ventricular fibrillation.

The presence of any ECG findings that are suspected to be caused by hyperkalemia should be considered a medical emergency.

If hyperkalemia is present or suspected, discontinue the infusion immediately and institute close ECG, laboratory and other monitoring and, as necessary, corrective therapy to reduce serum potassium concentrations.

Muscle weakness (up to and including muscular and respiratory paralysis, paresthesia of extremities) may occur as a complication of hyperkalemia.

- hyponatremia, manifestations may include seizures, coma, cerebral edema and death).
- hypernatremia, especially in patients with severe renal impairment.
- hypotension.
- gastrointestinal symptoms (ileus, nausea, vomiting, abdominal pain).
- fluid overload (which can lead to central and/or peripheral edema). See WARNINGS and ADVERSE REACTIONS.

When assessing an overdose, any additives in the solution must also be considered. The effects of an overdose may require immediate medical attention and treatment.

Interventions include discontinuation of Potassium Chloride in Sodium Chloride Injection, USP administration, dose reduction, and other measures as indicated for the specific clinical constellation (e.g., monitoring of fluid balance, electrolyte concentrations and acid base balance).

Dosage and Administration

Important Administration Instructions

- Potassium Chloride in Sodium Chloride Injection, USP is intended for intravenous infusion using sterile equipment.
- To avoid life threatening hyperkalemia, do not administer Potassium Chloride in Sodium Chloride Injection, USP as an intravenous push (i.e., intravenous injection manually with a syringe connected to the intravenous access) without a quantitative infusion device (see WARNINGS).
- Do not connect flexible plastic containers in series in order to avoid air embolism due to possible residual air contained in the primary container.
- Set the vent to the closed position on a vented intravenous administration set to prevent air embolism.
- Use a dedicated line without any connections to avoid air embolism.
- Do not pressurize intravenous solutions contained in flexible plastic containers to increase flow rates in order to avoid air embolism due to incomplete evacuation of residual air in the container.
- The choice of a central or peripheral venous route of infusion should depend on the osmolarity of the final infusate. Solutions with osmolarity of greater than or equal to approximately 900 mOsm/L must be infused through a central catheter.
- Prior to infusion, visually inspect the solution for particulate matter and discoloration. The solution should be clear and there should be no precipitates. Do not administer unless solution is clear and container is undamaged.
- Use of final filter is recommended during administration of all parenteral solutions, where possible.

Dosing Information

The choice of the specific potassium chloride and sodium chloride formulation, dosage, volume, rate and duration of administration is dependent upon the age, weight and clinical and metabolic condition of the patient and concomitant therapy, and administration should be determined by a physician experienced in intravenous fluid therapy.

Additional electrolyte supplementation may be indicated according to the clinical needs of the patient. Additives can be introduced to the container; however, some additives may be incompatible. Evaluate all additions to the plastic container for compatibility and stability of the resulting preparation. Consult with a pharmacist, if available.

If, in the informed judgment of the physician, it is deemed advisable to introduce additives, use aseptic technique. After addition, if there is a discoloration and/or the appearance of precipitates, insoluble complexes or crystals, do not use. Mix thoroughly when additives have been introduced. Do not store solutions containing additives. Discard any unused portion.

Rapid correction of hyponatremia and hypernatremia is potentially dangerous (risk of serious neurologic complications). To avoid complications such as osmotic demyelination syndrome (ODS) during administration, follow the important administration instructions, monitor serum sodium and chloride concentrations, fluid status, acid-base balance, and signs of neurologic complications.

HOW SUPPLIED

20 mEq/L Potassium Chloride in 0.45% Sodium Chloride Injection, USP is supplied in 1000 mL single-dose flexible plastic containers (NDC 0409-9257-39) (NDC 0990-9257-39).

ICU Medical is transitioning NDC codes from the "0409" to a "0990" labeler code. Both NDC codes are expected to be in the market for a period of time.

STORAGE AND HANDLING

Store at 20 to 25°C (68 to 77°F). [See USP Controlled Room Temperature.] Protect from freezing.

INSTRUCTIONS FOR USE

For information on risk of air embolism – see PRECAUTIONS.

To Open

Tear outer wrap at notch and remove solution container. If supplemental medication is desired, follow directions below before preparing for administration. Visually inspect the container. If the outlet port protector is damaged, detached, or not present, discard container as solution path sterility may be impaired. Some opacity of the plastic due to moisture absorption during the sterilization process may be observed. This is normal and does not affect the solution quality or safety. The opacity will diminish gradually.

Check for minute leaks by squeezing inner bag firmly. If leaks are found, discard solution as sterility may be impaired. If supplemental medication is desired, follow directions below.

To Add Medication

1. Prepare additive port.
2. Using aseptic technique and an additive delivery needle of appropriate length, puncture resealable additive port at target area, inner diaphragm and inject. Withdraw needle after injecting medication.
3. The additive port may be protected by covering with an additive cap.
4. Mix container contents thoroughly.

Preparation for Administration

(Use aseptic technique)

1. Close flow control clamp of administration set.
2. Remove cover from outlet port at bottom of container.
3. Insert piercing pin of administration set into port with a twisting motion until the set is firmly seated.
  NOTE: See full directions on administration set carton.
4. Suspend container from hanger.
5. Squeeze and release drip chamber to establish proper fluid level in chamber.
6. Open flow control clamp and clear air from set. Close clamp.
7. Attach set to venipuncture device. If device is not indwelling, prime and make venipuncture.
8. Regulate rate of administration with flow control clamp.

WARNING: Do not use flexible container in series connections.

Revised: July, 2022

ICU Medical, Inc., Lake Forest, Illinois, 60045, USA

IFU0000531

PRINCIPAL DISPLAY PANEL - 1000 mL Bag Label

20 mEq POTASSIUM

1000 mL

NDC 0990-9257-39

POTASSIUM
CHLORIDE
in 0.45%
Sodium Chloride
Injection, USP
20
mEq

EACH 100 mL CONTAINS POTASSIUM CHLORIDE 149 mg;
SODIUM CHLORIDE 450 mg IN WATER FOR INJECTION.
ELECTROLYTES PER 1000 mL: POTASSIUM 20 mEq;
SODIUM 77 mEq; CHLORIDE; 97 mEq.
194 mOsmol/LITER (CALC.)
pH 4.8 (3.5 to 6.5)

ADDITIVES MAY BE INCOMPATIBLE. CONSULT WITH
PHARMACIST, IF AVAILABLE. WHEN INTRODUCING
ADDITIVES, USE ASEPTIC TECHNIQUE,
MIX THOROUGHLY AND DO NOT STORE.

SINGLE-DOSE CONTAINER. STORE AT 20 TO 25°C (68 TO
77°F). [SEE USP CONTROLLED ROOM TEMPERATURE.]
PROTECT FROM FREEZING. FOR I.V. USE.
USUAL DOSAGE: SEE INSERT.
STERILE, NONPYROGENIC. USE ONLY IF SOLUTION IS
CLEAR AND CONTAINER IS UNDAMAGED. MUST NOT BE
USED IN SERIES CONNECTIONS.

Rx ONLY

3
V
CONTAINS DEHP

IMP0000058

ICU Medical, Inc.
Lake Forest, Illinois, 60045 USA

icumedical

PRINCIPAL DISPLAY PANEL - 1000 mL Bag Overwrap

TO OPEN TEAR AT NOTCH

2
HDPE

DO NOT REMOVE FROM OVERWRAP UNTIL READY FOR USE. AFTER REMOVING
THE OVERWRAP, CHECK FOR MINUTE LEAKS BY SQUEEZING CONTAINER FIRMLY.
IF LEAKS ARE FOUND, DISCARD SOLUTION AS STERILITY MAY BE IMPAIRED.
RECOMMENDED STORAGE: ROOM TEMPERATURE (25°C). AVOID EXCESSIVE
HEAT. PROTECT FROM FREEZING. SEE INSERT.
98-4321-R14-3/98